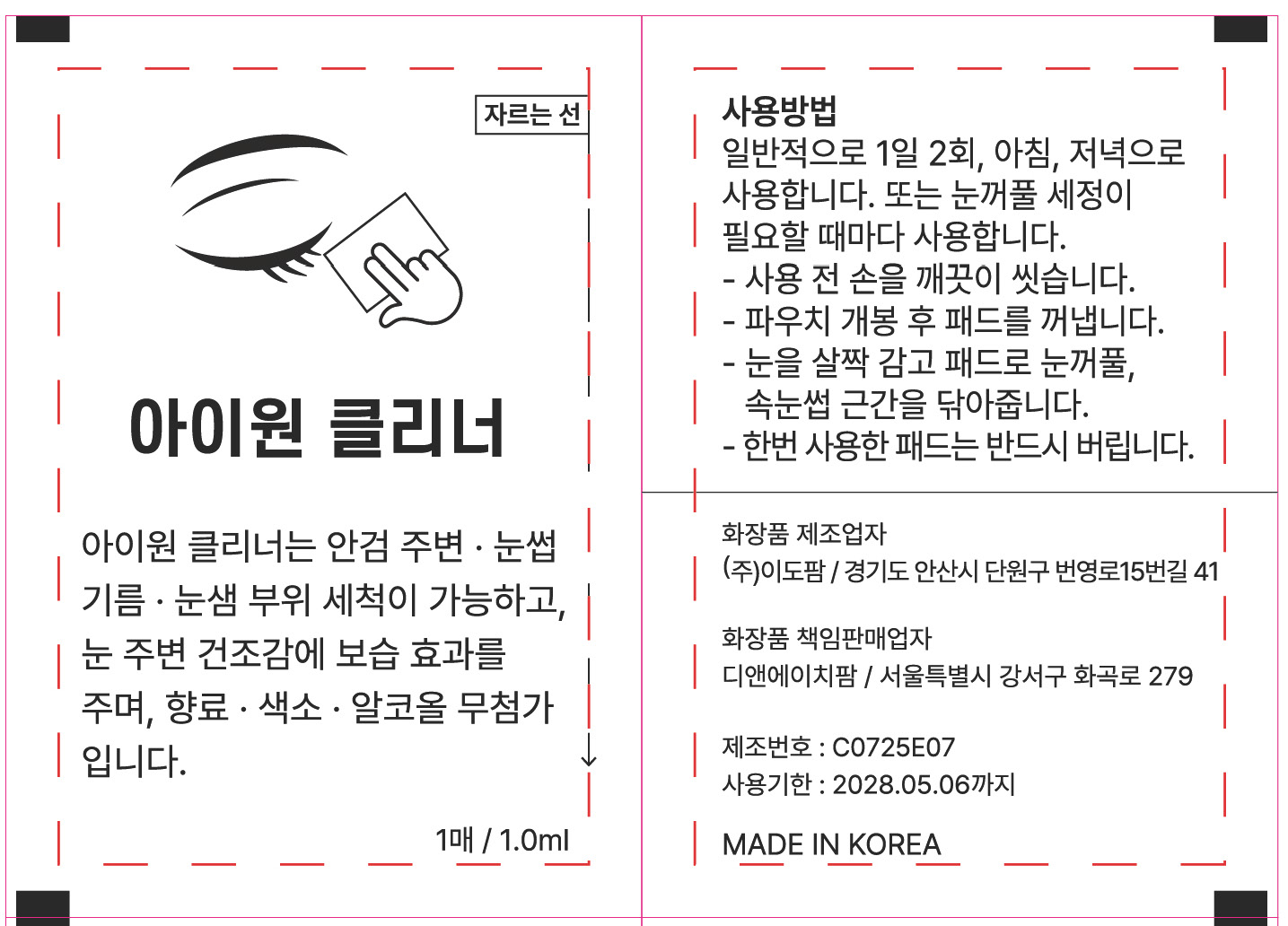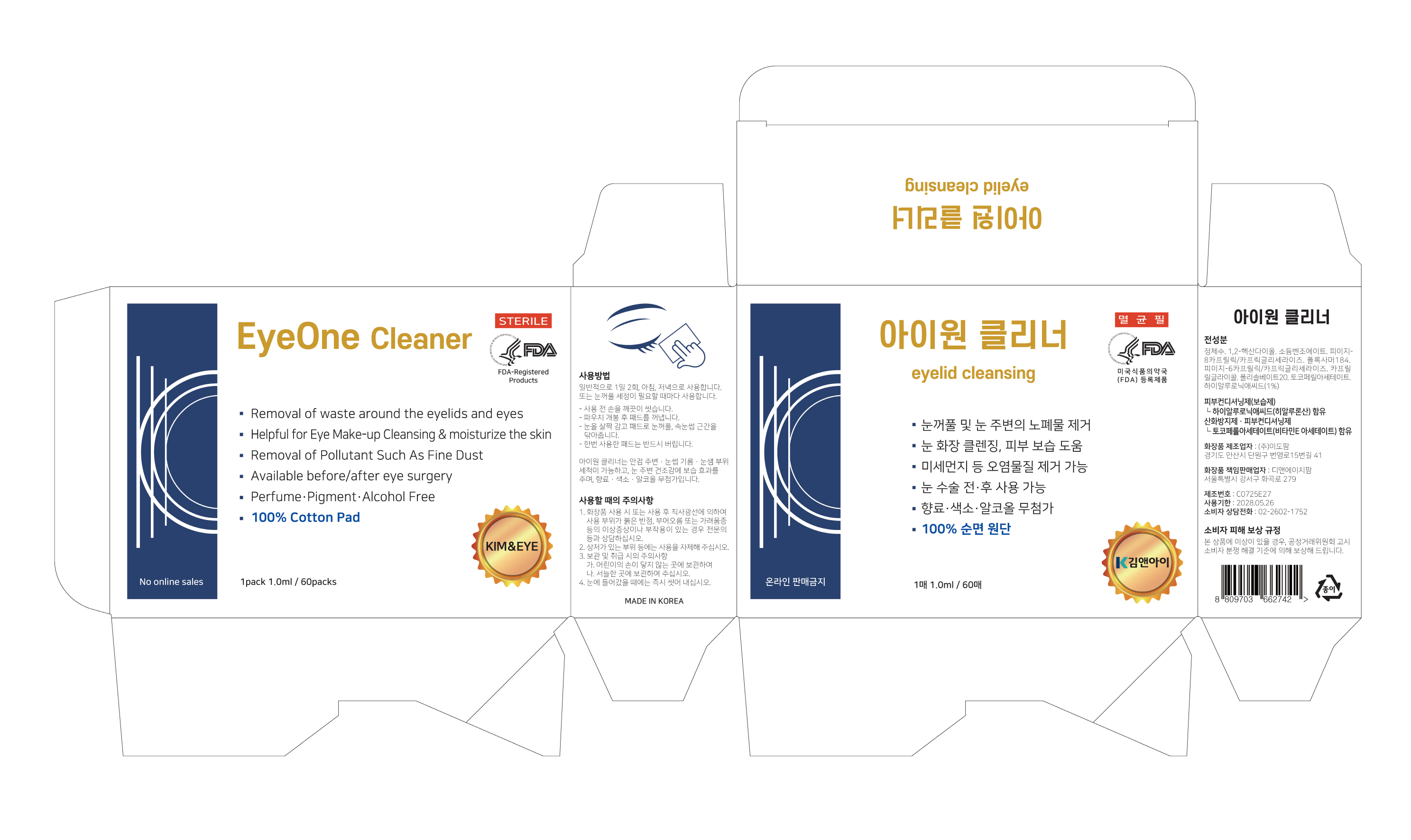 DRUG LABEL: EyeOne Cleaner
NDC: 77039-034 | Form: CLOTH
Manufacturer: IDO PHARM
Category: otc | Type: HUMAN OTC DRUG LABEL
Date: 20250610

ACTIVE INGREDIENTS: ALPHA-TOCOPHEROL ACETATE 0.00001 g/1 mL; HYALURONIC ACID 0.0000001 g/1 mL
INACTIVE INGREDIENTS: CAPRYLYL GLYCOL; 1,2-HEXANEDIOL; PEG-8 CAPRYLIC/CAPRIC GLYCERIDES; PEG-6 CAPRYLIC/CAPRIC GLYCERIDES; POLOXAMER 184; CAPRYLOYL GLYCINE; POLYSORBATE 20; WATER

ACTIVE INGREDIENT

Hyaluronic acid, Tocopheryl Acetate

PURPOSE

It cleans the area of eyebrow oil and glands and moisturizes the dryness around the eyes

INDICATIONS AND USAGE

Use it whenever you need to clean your eyelids

WARNINGS

1. Consult a specialist if you have abnormal symptoms or side effects such as red spots, swelling, or itching due to direct sunlight during or after using this product.
2. Please refrain from using the wound area
3. Precautions for Storage and Handling
A. Please keep it out of the reach of children.
B. Please store it in a cool place.
4. Wash it immediately when it gets into your eyes.

keep it out of the reach of children.

INACTIVE INGREDIENT

WATER,1,2-Hexanediol, Sodium Benzoate, PEG-8 CAPRYLIC/CAPRIC GLYCERIDES, PEG-6 CAPRYLIC/CAPRIC GLYCERIDES, POLOXAMER 184, Caprylyl Glycol, POLYSORBATE 20

DOSAGE AND ADMINISTRATION

It is generally used twice a day, in the morning and evening.
Or use it whenever you need to clean your eyelids.
- Wash your hands thoroughly before use.
- Remove the pad after opening the packet.
- Close your eyes and wipe the eyelids and the base of your eyelashes with cloth.
- Once used, throw away cloth without fail.